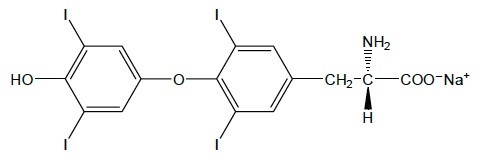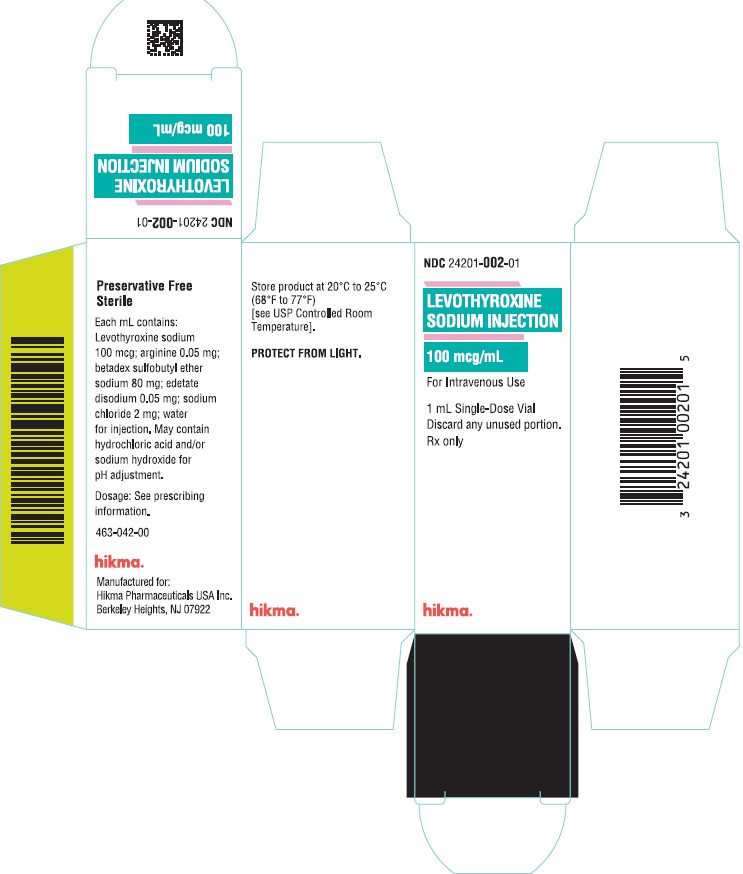 DRUG LABEL: Levothyroxine Sodium
NDC: 24201-002 | Form: INJECTION, SOLUTION
Manufacturer: Hikma Pharmaceuticals USA Inc.
Category: prescription | Type: HUMAN PRESCRIPTION DRUG LABEL
Date: 20240710

ACTIVE INGREDIENTS: LEVOTHYROXINE SODIUM 100 ug/1 mL
INACTIVE INGREDIENTS: ARGININE; EDETATE DISODIUM; BETADEX SULFOBUTYL ETHER SODIUM; SODIUM CHLORIDE; SODIUM HYDROXIDE; HYDROCHLORIC ACID; WATER

HIGHLIGHTS OF PRESCRIBING INFORMATION

These highlights do not include all the information needed to use LEVOTHYROXINE SODIUM INJECTION safely and effectively. See full prescribing information for LEVOTHYROXINE SODIUM INJECTION
LEVOTHYROXINE SODIUM injection, for intravenous use
Initial U.S. Approval: 1969

WARNING: NOT FOR TREATMENT OF OBESITY OR FOR WEIGHT LOSS

Thyroid hormones, including Levothyroxine Sodium Injection, should not be used for the treatment of obesity or for weight loss. (5.3) Larger doses may produce serious or even life-threatening manifestations of toxicity. (6)

1 INDICATIONS AND USAGE

Levothyroxine Sodium is an L-thyroxine product. Levothyroxine (T4) Sodium Injection is indicated for the treatment of myxedema coma. (1)

Important Limitations of Use:

The relative bioavailability of this drug has not been established. Use caution when converting patients from oral to intravenous levothyroxine. (1)

2 DOSAGE AND ADMINISTRATION

- Consider the patient’s age, general physical condition, cardiac risk factors, as well as the clinical severity of myxedema and duration of myxedema symptoms when determining dosages of Levothyroxine Sodium Injection. (2.1)
- Start with lower doses in elderly patients and in patients with underlying cardiovascular disease. (2.1)
- An initial intravenous loading dose of Levothyroxine Sodium Injection between 300 to 500 mcg followed by once daily intravenous maintenance doses between 50 and 100 mcg should be administered, as clinically indicated, until the patient can tolerate oral therapy. (2.1)
- Do not add to other IV fluids. (2.2)

3 DOSAGE FORMS AND STRENGTHS

Injection: 100 mcg/mL in a single-dose vial. Ready-to-use solution. (3)

4 CONTRAINDICATIONS

None

5 WARNINGS AND PRECAUTIONS

- Cardiac Adverse Reactions in the Elderly and in Patients with Underlying Cardiovascular Disease: Overtreatment may cause arrhythmias, tachycardia, myocardial ischemia and infarction, or worsening of congestive heart failure and death, particularly in patients with cardiovascular disease and in elderly patients. Start with lower doses in elderly patients and in patients with underlying cardiovascular disease and monitor patients after administration (5.1).
- Acute Adrenal Crisis in Patients with Concomitant Adrenal Insufficiency Initiation of thyroid hormone therapy prior to initiating glucocorticoid therapy may precipitate an acute adrenal crisis in patients with adrenal insufficiency. Treat patients with adrenal insufficiency with replacement glucocorticoids prior to initiating treatment (5.2).
- Worsening of Diabetic Control: May worsen glycemic control and result in increased antidiabetic agent or insulin requirements. Carefully monitor glycemic control (5.3)

6 ADVERSE REACTIONS

Adverse reactions associated with Levothyroxine Sodium Injection are primarily those of hyperthyroidism due to therapeutic overdosage: fatigue, increased appetite, weight loss, heat intolerance, fever, excessive sweating, headache, hyperactivity, nervousness, anxiety, irritability, emotional lability, insomnia, tremors, muscle weakness, muscle spasm, palpitations, tachycardia, arrhythmias, increased pulse and blood pressure, heart failure, angina, myocardial infarction, cardiac arrest, dyspnea, diarrhea, vomiting, abdominal cramps, elevations in liver function tests, flushing, and rash. (6)

To report SUSPECTED ADVERSE REACTIONS, contact Hikma at us.hikma@primevigilance.com or call 1-877-845-0689 or FDA at 1-800-FDA-1088 or www.fda.gov/medwatch.

7 DRUG INTERACTIONS

Many drugs affect thyroid hormone pharmacokinetics and metabolism (e.g., absorption, synthesis, secretion, catabolism, protein binding, and target tissue response) and may alter the therapeutic response to Levothyroxine Sodium Injection. (7, 12.3)

8 USE IN SPECIFIC POPULATIONS

Elderly and those with underlying cardiovascular disease should receive doses at the lower end of the recommended range. (8.5)

FULL PRESCRIBING INFORMATION

WARNING: NOT FOR TREATMENT OF OBESITY OR FOR WEIGHT LOSS

Thyroid hormones, including Levothyroxine Sodium Injection, should not be used for the treatment of obesity or for weight loss. (5.3)

Larger doses may produce serious or even life-threatening manifestations of toxicity. (6)

1 INDICATIONS AND USAGE

Levothyroxine Sodium Injection is indicated for the treatment of myxedema coma.

Limitations of Use: The relative bioavailability between Levothyroxine Sodium Injection and oral levothyroxine products has not been established. Caution should be used when switching patients from oral levothyroxine products to Levothyroxine Sodium Injection as accurate dosing conversion has not been studied.

2 DOSAGE AND ADMINISTRATION

2.1 Dosage

An initial intravenous loading dose of Levothyroxine Sodium Injection between 300 to 500 mcg, followed by once daily intravenous maintenance doses between 50 and 100 mcg, should be administered, as clinically indicated, until the patient can tolerate oral therapy.

The age, general physical condition, and cardiac risk factors of the patient, as well as the clinical severity of myxedema and duration of myxedema symptoms should be considered when determining the starting and maintenance dosages of Levothyroxine Sodium Injection.

Levothyroxine Sodium Injection produces a gradual increase in the circulating concentrations of the hormone with an approximate half-life of 9 to 10 days in hypothyroid patients. Daily administration of Levothyroxine Sodium Injection should be maintained until the patient is capable of tolerating an oral dose and is clinically stable. For chronic treatment of hypothyroidism, an oral dosage form of levothyroxine should be used to maintain a euthyroid state. Relative bioavailability between Levothyroxine Sodium Injection and oral levothyroxine products has not been established. Based on medical practice, the relative bioavailability between oral and intravenous administration of Levothyroxine Sodium Injection is estimated to be from 48 to 74%. Due to differences in absorption characteristics of patients and the oral levothyroxine product formulations, TSH and thyroid hormone levels should be measured a few weeks after initiating oral levothyroxine and dose adjusted accordingly.

2.2 Dosing in the Elderly and in Patients with Cardiovascular Disease

Intravenous levothyroxine may be associated with cardiac toxicity – including arrhythmias, tachycardia, myocardial ischemia and infarction, or worsening of congestive heart failure and death – in the elderly and in those with underlying cardiovascular disease. Therefore, cautious use, including doses in the lower end of the recommended range, may be warranted in these populations.

2.3 Administration Instructions

Intravenous levothyroxine may be associated with cardiac toxicity-including arrhythmias, tachycardia, myocardial ischemia and infarction, or worsening of congestive heart failure and death—in the elderly and in those with underlying cardiovascular disease. Therefore, cautious use, including doses in the lower end of the recommended range, may be warranted in these populations.

Discard any unused portion. DO NOT ADD LEVOTHYROXINE SODIUM INJECTION TO OTHER INTRAVENOUS FLUIDS. Parenteral drug products should be inspected visually for particulate matter and discoloration prior to administration, whenever solution and container permit.

3 DOSAGE FORMS AND STRENGTHS

Levothyroxine sodium injection 100 mcg/mL is a clear, colorless to slightly yellow solution supplied as 1 mL per vial.

4 CONTRAINDICATIONS

None

5 WARNINGS AND PRECAUTIONS

5.1 Risk of Cardiac Complications in Elderly and in Patients with Cardiovascular Disease

Excessive bolus dosing of Levothyroxine Sodium Injection (greater than 500 mcg) is associated with cardiac complications, particularly in the elderly and in patients with an underlying cardiac condition. Adverse events that can potentially be related to the administration of large doses of Levothyroxine Sodium Injection include arrhythmias, tachycardia, myocardial ischemia and infarction, or worsening of congestive heart failure and death. Cautious use, including doses in the lower end of the recommended range, may be warranted in these populations. Close observation of the patient following the administration of Levothyroxine Sodium Injection is advised.

5.2 Acute Adrenal Crisis in Patients with Concomitant Adrenal Insufficiency

Chronic autoimmune thyroiditis, which can lead to myxedema coma, may occur in association with other autoimmune disorders such as adrenal insufficiency, pernicious anemia, and insulin‑dependent diabetes mellitus. Patients should be treated with replacement glucocorticoids prior to initiation of treatment with Levothyroxine Sodium Injection, until adrenal function has been adequately assessed. Failure to do so may precipitate an acute adrenal crisis when thyroid hormone therapy is initiated, due to increased metabolic clearance of glucocorticoids by thyroid hormone. With initiation of Levothyroxine Sodium Injection, patients with myxedema coma should also be monitored for previously undiagnosed diabetes insipidus.

5.3 Worsening of Diabetic Control

Addition of levothyroxine therapy in patients with diabetes mellitus may worsen glycemic control and result in increased antidiabetic agent or insulin requirements. Carefully monitor glycemic control [see Drug Interactions (7.1)].

6 ADVERSE REACTIONS

Adverse reactions associated with levothyroxine are primarily those of hyperthyroidism due to therapeutic overdosage [see Warnings and Precautions (5), Overdosage (10)]. They include the following:

- General: fatigue, increased appetite, weight loss, heat intolerance, fever, excessive sweating
- Central nervous system: headache, hyperactivity, nervousness, anxiety, irritability, emotional lability, insomnia
- Musculoskeletal: tremors, muscle weakness, muscle spasm
- Cardiovascular: palpitations, tachycardia, arrhythmias, increased pulse and blood pressure, heart failure, angina, myocardial infarction, cardiac arrest
- Respiratory: dyspnea
- Gastrointestinal: diarrhea, vomiting, abdominal cramps, elevations in liver function tests
- Dermatologic: flushing, rash

Seizures have been reported rarely with the institution of levothyroxine therapy.

Hypersensitivity Reactions

Hypersensitivity reactions to inactive ingredients have occurred in patients treated with thyroid hormone products. These include urticaria, pruritus, skin rash, flushing, angioedema, various gastrointestinal symptoms (abdominal pain, nausea, vomiting and diarrhea), fever, arthralgia, serum sickness, and wheezing. Hypersensitivity to levothyroxine itself is not known to occur.

7 DRUG INTERACTIONS

7.1 Drugs Known to Affect Thyroid Hormone Pharmacokinetics

Many drugs affect thyroid hormone pharmacokinetics and metabolism (e.g., synthesis, secretion, catabolism, protein binding, and target tissue response) and may alter the therapeutic response to Levothyroxine Sodium Injection (see Tables 1-3).

Table 1: Drugs That May Alter T4 and Triiodothyronine (T3) Serum Transport Without Effecting Free Thyroxine (FT4) Concentration (Euthyroidism)
Drug or Drug Class | Effect
Clofibrate; Estrogen-containing oral contraceptives; Estrogens (oral); Heroin/Methadone; 5-Fluorouracil; Mitotane; Tamoxifen | These drugs may increase serum thyroxine-binding globulin (TBG) concentration.
Androgens/Anabolic Steroids; Asparaginase; Glucocorticoids; Slow-Release Nictonic Acid | These drugs may decrease serum TBG concentration.
Potential impact (below): Administration of these agents with levothyroxine results in an initial transient increase in FT4. Continued administration results in a decrease in serum T4 and normal FT4 and TSH concentrations.
Salicylates (> 2 g/day) | Salicylates inhibit binding of T4 and T3 to TBG and transthyretin. An initial increase in serum FT4 is followed by return of FT4 to normal levels with sustained therapeutic serum salicylate concentrations, although total T4 levels may decrease by as much as 30%.
Other drugs:; Carbamazepine; Furosemide (> 80 mg IV); Heparin; Hydantoins; Non-Steroidal Anti-Inflammatory Drugs; - Fenamates | These drugs may cause protein-binding site displacement. Furosemide has been shown to inhibit the protein binding of T4 to TBG and albumin, causing an increase free T4 fraction in serum. Furosemide competes for T4-binding sites on TBG, prealbumin, and albumin, so that a single high dose can acutely lower the total T4 level. Phenytoin and carbamazepine reduce serum protein binding of levothyroxine, and total and free T4 may be reduced by 20% to 40%, but most patients have normal serum TSH levels and are clinically euthyroid. Closely monitor thyroid hormone parameters.

Table 2: Drugs That May Alter Hepatic Metabolism of T4 (Hypothyroidism)
Potential impact: Stimulation of hepatic microsomal drug-metabolizing enzyme activity may cause increased hepatic degradation of levothyroxine, resulting in increased levothyroxine requirements.
Drug or Drug Class | Effect
Phenobarbital Rifampin | Phenobarbital has been shown to reduce the response to thyroxine. Phenobarbital increases L-thyroxine metabolism by inducing uridine 5’-diphospho-glucuronosyltransferase (UGT) and leads to a lower T4 serum levels. Changes in thyroid status may occur if barbiturates are added or withdrawn from patients being treated for hypothyroidism. Rifampin has been shown to accelerate the metabolism of levothyroxine.

Table 3: Drugs That May Decrease Conversion of T4 to T3
Potential impact: Administration of these enzyme inhibitors decreases the peripheral conversion of T4 to T3, leading to decreased T3 levels. However, serum T4 levels are usually normal but may occasionally be slightly increased.
Drug or Drug Class | Effect
Beta-adrenergic antagonists; e.g., Propranolol > 160 mg/day) | In patients treated with large doses of propranolol (> 160 mg/day), T3 and T4 levels change slightly, TSH levels remain normal, and patients are clinically euthyroid. It should be noted that actions of particular beta-adrenergic antagonists may be impaired when the hypothyroid patient is converted to the euthyroid state.
Glucocorticoids (e.g., Dexamethasone ≥ 4 mg/day) | Short-term administration of large doses of glucocorticoids may decrease serum T3 concentrations by 30% with minimal change in serum T4 levels. However, long-term glucocorticoid therapy may result in slightly decreased T3 and T4 levels due to decreased TBG production (See above).
Other drugs: Amiodarone | Amiodarone inhibits peripheral conversion of levothyroxine (T4) to triiodothyronine (T3) and may cause isolated biochemical changes (increase in serum free-T4, and decreased or normal free-T3) in clinically euthyroid patients.

7.2 Antidiabetic Therapy

Addition of levothyroxine to antidiabetic or insulin therapy may result in increased antidiabetic agent or insulin requirements. Careful monitoring of diabetic control is recommended.

7.3 Oral Anticoagulants

Levothyroxine increases the response to oral anticoagulant therapy. Therefore, a decrease in the dose of anticoagulant may be warranted with correction of the hypothyroid. Closely monitor coagulation tests to permit appropriate and timely dosage adjustments.

7.4 Digitalis Glycosides

Levothyroxine may reduce the therapeutic effects of digitalis glycosides. Serum digitalis glycoside levels may be decreased when a hypothyroid patient becomes euthyroid, necessitating an increase in the dose of digitalis glycosides.

7.5 Antidepressant Therapy

Concurrent use of tricyclic (e.g., amitriptyline) or tetracyclic (e.g., maprotiline) antidepressants and levothyroxine may increase the therapeutic and toxic effects of both drugs, possibly due to increased receptor sensitivity to catecholamines. Toxic effects may include increased risk of cardiac arrhythmias and central nervous system stimulation. Levothyroxine may accelerate the onset of action of tricyclics. Administration of sertraline in patients stabilized on levothyroxine may result in increased levothyroxine requirements.

7.6 Ketamine

Concurrent use of ketamine and levothyroxine may produce marked hypertension and tachycardia. Closely monitor blood pressure and heart rate in these patients.

7.7 Sympathomimetics

Concurrent use may of sympathomimetics and levothyroxine may increase the effects of sympathomimetics or thyroid hormone. Thyroid hormones may increase the risk of coronary insufficiency when sympathomimetic agents are administered to patients with coronary artery disease.

7.8 Drug-Laboratory Test Interactions

Consider changes in TBG concentration when interpreting T4 and T3 values. Measure and evaluate unbound (free) hormone and/or determine the free T4 index (FT4I) in this circumstance. Pregnancy, infectious hepatitis, estrogens, estrogen containing oral contraceptives, and acute intermittent porphyria increase TBG concentrations. Nephrosis, severe hypoproteinemia, severe liver disease, acromegaly, androgens, and corticosteroids decrease TBG concentration. Familial hyper- or hypo-thyroxine binding globulinemias have been described, with the incidence of TBG deficiency approximating 1 in 9000.

8 USE IN SPECIFIC POPULATIONS

8.1 Pregnancy

Risk Summary

The clinical data in pregnant women treated with oral levothyroxine to treat hypothyroidism do not indicate a drug-associated risk of major birth defects, miscarriage, or adverse maternal or fetal outcomes. There are no data available on the use of Levothyroxine Sodium Injection in pregnant women. There are risks to the mother and fetus associated with myxedema coma in pregnancy (see Clinical Considerations).

No developmental or reproductive toxicity studies in animals have been conducted with Levothyroxine Sodium Injection.

The estimated background risks of major birth defects and miscarriage for the indicated populations are unknown. All pregnancies have background risks of birth defect, loss, or other adverse outcomes. In the U.S. general population, the estimated background risks of major birth defects and miscarriage in clinically recognized pregnancies are 2 to 4% and 15 to 20%, respectively.

Clinical Considerations

Disease-Associated Maternal and/or Embryo/Fetal Risk

Myxedema coma is a medical emergency that can be fatal if left untreated. Delaying treatment in pregnant women with myxedema coma increases the risk of maternal and fetal morbidity and mortality. Life-sustaining therapy for pregnant women with myxedema coma should not be withheld due to potential concerns regarding the effects of Levothyroxine Sodium Injection on the fetus.

8.2 Lactation

Risk Summary

Published studies report that levothyroxine is present in human milk following the administration of oral levothyroxine. No adverse effects on the breastfed infant have been reported, and there is no information on the effects of levothyroxine on milk production from levothyroxine oral treatment. There are no available data with use of Levothyroxine Sodium Injection in lactating women. The developmental and health benefits of breastfeeding should be considered along with the mother's clinical need for Levothyroxine Sodium Injection and any potential adverse effects on the breastfed infant from Levothyroxine Sodium Injection or from the underlying maternal condition.

8.4 Pediatric Use

The safety and effectiveness of Levothyroxine Sodium Injection have not been established in pediatric patients.

8.5 Geriatric Use and Patients with Underlying Cardiovascular Disease

See Section 2, Dosage and Administration, for full prescribing information in the geriatric patient population. Because of the increased prevalence of cardiovascular disease in the elderly, cautious use of Levothyroxine Sodium Injection in the elderly and in patients with known cardiac risk factors is advised. Atrial fibrillation is a common side effect associated with levothyroxine treatment in the elderly [see Dosage and Administration (2) and Warnings and Precautions (5)].

8.6 Renal Impairment

Serum creatinine and levothyroxine levels should be closely monitored in patients with severe renal impairment receiving intravenous levothyroxine with betadex sulfobutyl (SBECD) [See Clinical Pharmacology (12.3)].

10 OVERDOSAGE

In general, the signs and symptoms of overdosage with levothyroxine are those of hyperthyroidism [see Warnings and Precautions (5) and Adverse Reactions (6)]. In addition, confusion and disorientation may occur. Cerebral embolism, shock, coma, and death have been reported. Excessive doses of Levothyroxine Sodium Injection (greater than 500 mcg) are associated with cardiac complications in patients with underlying cardiac disease.

Treatment of Overdosage

Levothyroxine Sodium Injection should be reduced in dose or temporarily discontinued if signs or symptoms of overdosage occur. To obtain up-to-date information about the treatment of overdose, a good resource is the certified Regional Poison Control Center. In managing overdosage, consider the possibility of multiple drug overdoses, interaction among drugs, and unusual drug kinetics in the patient.

In the event of an overdose, appropriate supportive treatment should be initiated as dictated by the patient’s medical status.

11 DESCRIPTION

Levothyroxine sodium injection contains synthetic levothyroxine (L-thyroxine) sodium salt. Levothyroxine sodium has an empirical formula of C15H10I4NNaO4, a molecular weight of 798.85 g/mol (anhydrous), and the following structural formula:

Levothyroxine sodium injection is a sterile, preservative-free, clear, colorless to slightly yellow solution for intravenous administration available as 100 mcg/mL in a single-dose clear glass vial. Each mL of levothyroxine sodium injection also contains 0.05 mg arginine, USP; 80 mg betadex sulfobutyl ether sodium, USP; 0.05 mg edetate disodium, USP; and water for injection, USP. Sodium chloride, USP was added to adjust tonicity. Hydrochloric acid, NF and/or sodium hydroxide, NF may have been added for pH adjustment.

12 CLINICAL PHARMACOLOGY

12.1 Mechanism of Action

Thyroid hormones exert their physiologic actions through control of DNA transcription and protein synthesis. Triiodothyronine (T3) and levothyroxine (T4) diffuse into the cell nucleus and bind to thyroid receptor proteins attached to DNA. This hormone nuclear receptor complex activates gene transcription and synthesis of messenger RNA and cytoplasmic proteins.

The physiological actions of thyroid hormones are produced predominantly by T3, the majority of which (approximately 80%) is derived from T4 by deiodination in peripheral tissues.

12.2 Pharmacodynamics

Thyroid hormone synthesis and secretion is regulated by the hypothalamic pituitary-thyroid axis. Thyrotropin releasing hormone (TRH) released from the hypothalamus stimulates secretion of thyrotropin stimulating hormone (TSH) from the anterior pituitary. TSH, in turn, is the physiologic stimulus for the synthesis and secretion of thyroid hormones, T4 and T3, by the thyroid gland. Circulating serum T3 and T4 levels exert a feedback effect on both TRH and TSH secretion. When serum T3 and T4 levels increase, TRH and TSH secretion decrease. When thyroid hormone levels decrease, TRH and TSH secretion increases. TSH is used for the diagnosis of hypothyroidism and evaluation of levothyroxine therapy adequacy with other laboratory and clinical data [see Dosage (2.1)]. There are drugs known to affect thyroid hormones and TSH by various mechanisms and those examples are diazepam, ethioamide, lovastatin, metoclopramide, 6-mercaptopurine, nitroprusside, perphenazine, and thiazide diuretics. Some drugs may cause a transient decrease in TSH secretion without hypothyroidism and those drugs (dose) are dopamine (greater than 1 mcg per kg per min), glucocorticoids (hydrocortisone greater than 100 mg per day or equivalent) and octreotide (greater than 100 mcg per day).

Thyroid hormones regulate multiple metabolic processes and play an essential role in normal growth and development, and normal maturation of the central nervous system and bone. The metabolic actions of thyroid hormones include augmentation of cellular respiration and thermogenesis, as well as metabolism of proteins, carbohydrates and lipids. The protein anabolic effects of thyroid hormones are essential to normal growth and development.

12.3 Pharmacokinetics

Absorption – Levothyroxine Sodium Injection is administered via the intravenous route. Following administration, the synthetic levothyroxine cannot be distinguished from the natural hormone that is secreted endogenously.

Distribution – Circulating thyroid hormones are greater than 99% bound to plasma proteins, including thyroxine binding globulin (TBG), thyroxine binding prealbumin (TBPA), and albumin (TBA), whose capacities and affinities vary for each hormone. The higher affinity of both TBG and TBPA for T4 partially explains the higher serum levels, slower metabolic clearance, and longer half-life of T4 compared to T3. Protein bound thyroid hormones exist in reverse equilibrium with small amounts of free hormone. Only unbound hormone is metabolically active. Many drugs and physiologic conditions affect the binding of thyroid hormones to serum proteins [see Warnings and Precautions (5) and Drug Interactions (7)]. Thyroid hormones do not readily cross the placental barrier [see Warnings and Precautions (5) and Use in Specific Populations (8)]. Betadex sulfobutyl ether (SBECD) does not affect levothyroxine binding to plasma proteins.

Metabolism – T4 is slowly eliminated. The major pathway of thyroid hormone metabolism is through sequential deiodination. Approximately eighty percent of circulating T3 is derived from peripheral T4 by mono-deiodination. The liver is the major site of degradation for both T4 and T3, with T4 deiodination also occurring at a number of additional sites, including the kidney and other tissues. Approximately 80% of the daily dose of T4 is deiodinated to yield equal amounts of T3 and reverse T3 (rT3). T3 and rT3 are further deiodinated to diiodothyronine. Thyroid hormones are also metabolized via conjugation with glucuronides and sulfates and excreted directly into the bile and gut where they undergo enterohepatic recirculation.

Elimination – Thyroid hormones are primarily eliminated by the kidneys. A portion of the conjugated hormone reaches the colon unchanged, where it is hydrolyzed and eliminated in feces as the free hormones. Urinary excretion of T4 decreases with age.

In patients with severe renal impairment or ESRD (eGFR of < 15 mL/min/1.73 m2), accumulation of SBECD occurs [see Renal Impairment 8.6].

Table 1: Pharmacokinetic Parameters of Thyroid Hormones in Euthyroid Patients

Hormone | Ratio in Thyroglobulin | Biologic Potency | Half-Life (Days) | Protein Binding (%)^2
T4 | 10 to 20 | 1 | 6 to 8^1 | 99.96
T3 | 1 | 4 | ≤ 2 | 99.5

T4: Levothyroxine

T3: Liothyronine
^13 to 4 days in hyperthyroidism, 9 to 10 days in hypothyroidism.
^2Includes TBG, TBPA, and TBA.

13 NONCLINICAL TOXICOLOGY

13.1 Carcinogenesis, Mutagenesis, Impairment of Fertility

Animal studies have not been performed to evaluate the carcinogenic potential, mutagenic potential or effects on fertility of Levothyroxine Sodium Injection.

13.2 Animal Toxicology and Pharmacology

No animal toxicology studies have been conducted with Levothyroxine Sodium Injection.

14 CLINICAL STUDIES

No clinical studies have been conducted with Levothyroxine Sodium Injection in patients with myxedema coma. However, data from published literature support the intravenous use of levothyroxine sodium for the treatment of myxedema coma.

16 HOW SUPPLIED/STORAGE AND HANDLING

16.1 How Supplied

Levothyroxine Sodium Injection 100 mcg/mL is a clear, colorless to slightly yellow solution, supplied as1 mL per vial.

Package of 1 single-dose vial: NDC 24201-002-01

16.2 Storage and Handling

Protect from light and store product at 20° to 25°C (68° to 77°F) [see USP Controlled Room Temperature]. Drug product is preservative free. Discard any unused portion.

Manufactured for:

Hikma Pharmaceuticals USA Inc.

Berkeley Heights, NJ 07922

www.hikma.com/us

Revised: 07/2024

462-046-00

Principal Display Panel

NDC 24201-002-01
Levothyroxine
Sodium Injection
100 mcg/mL

For Intravenous Use
1 mL Single-Dose Vial

Discard any unused portion.
Rx only